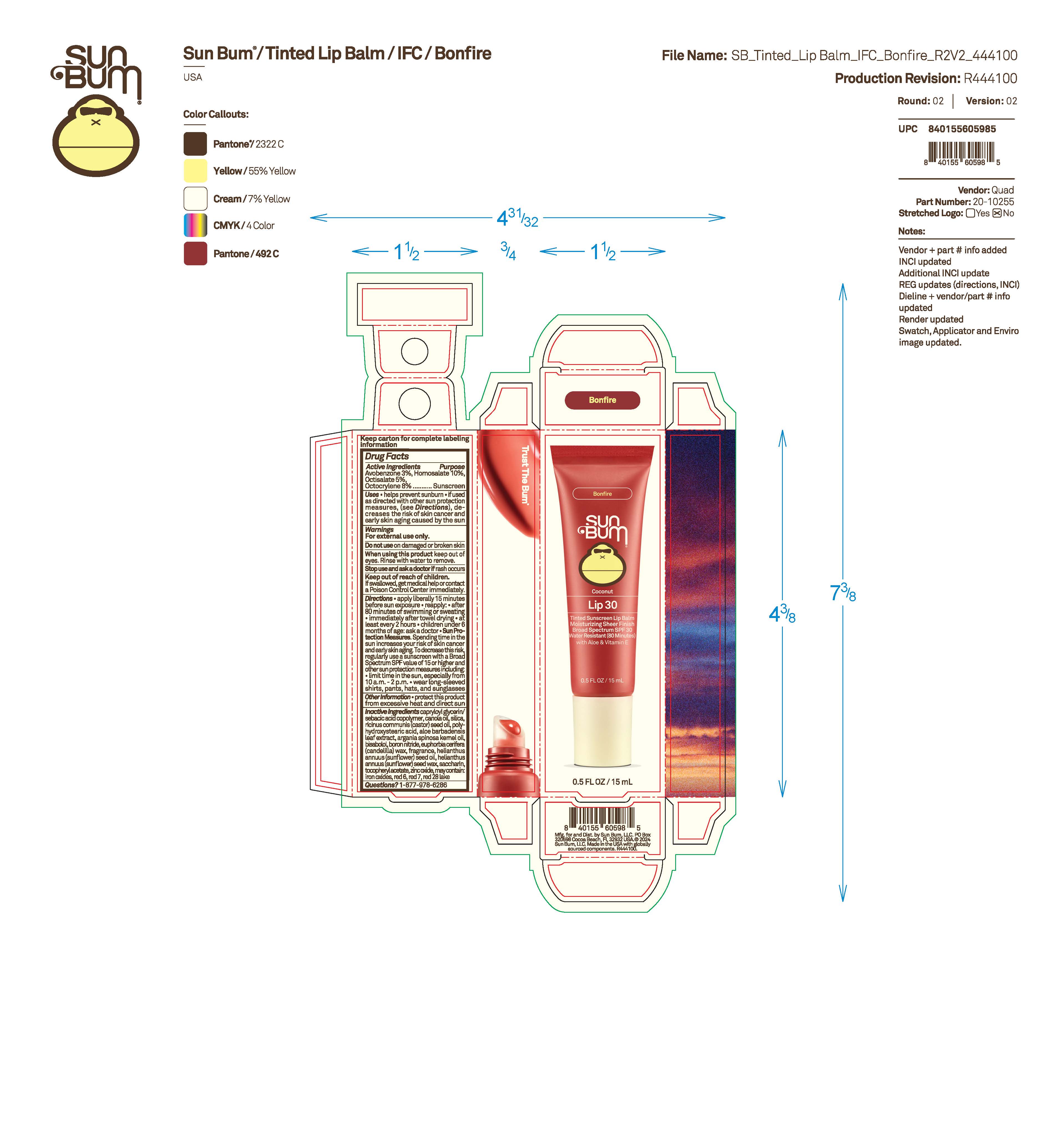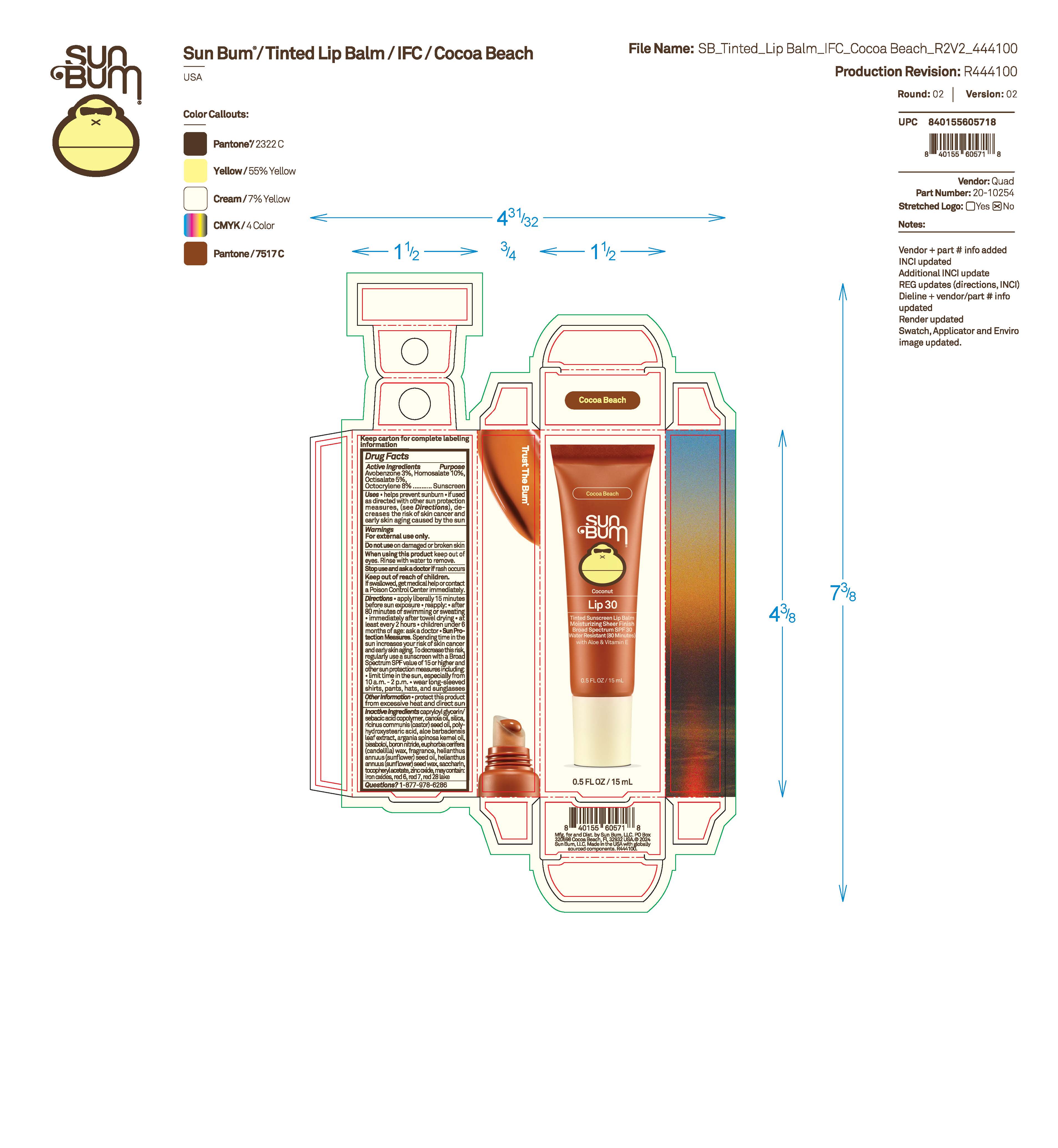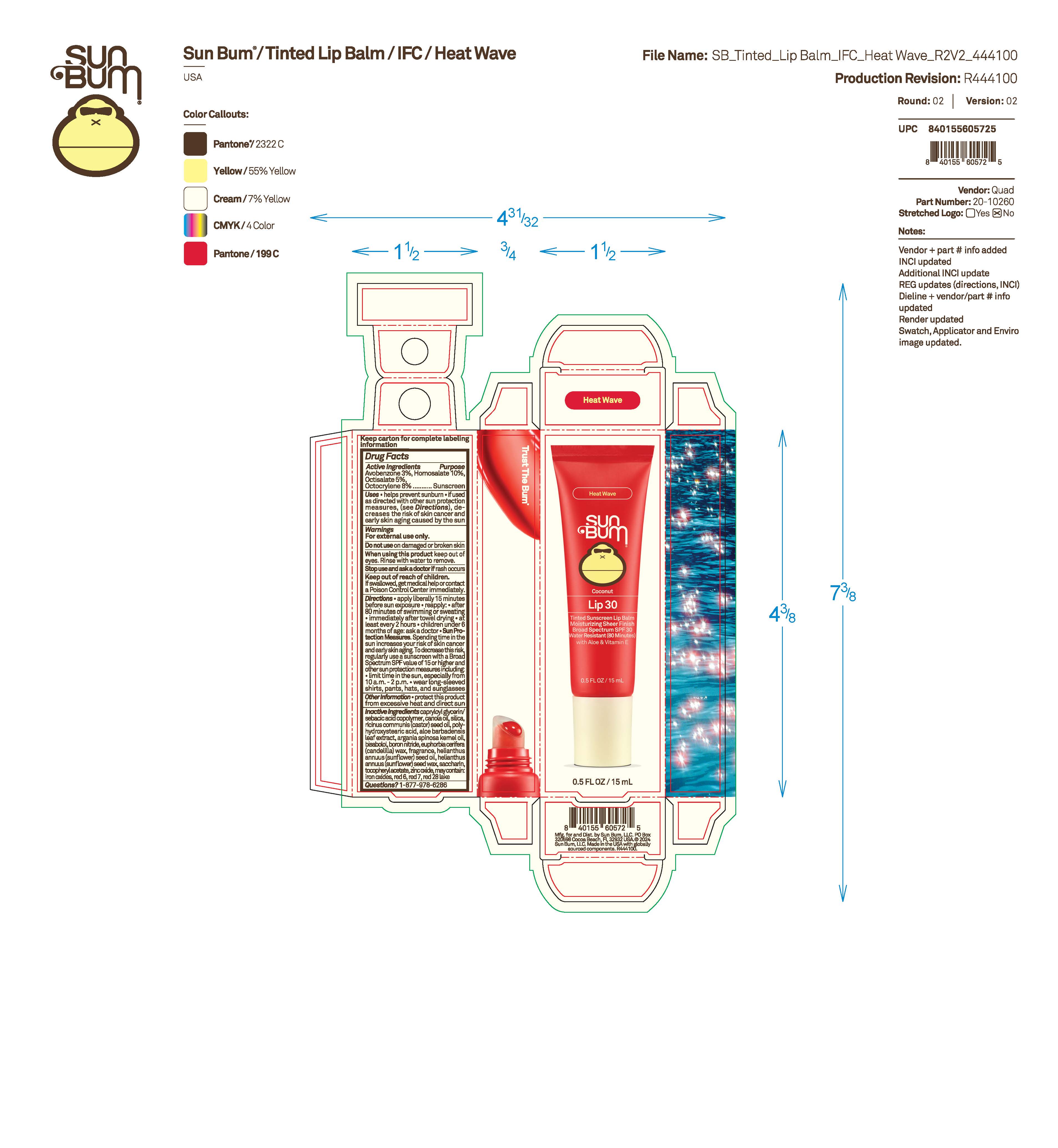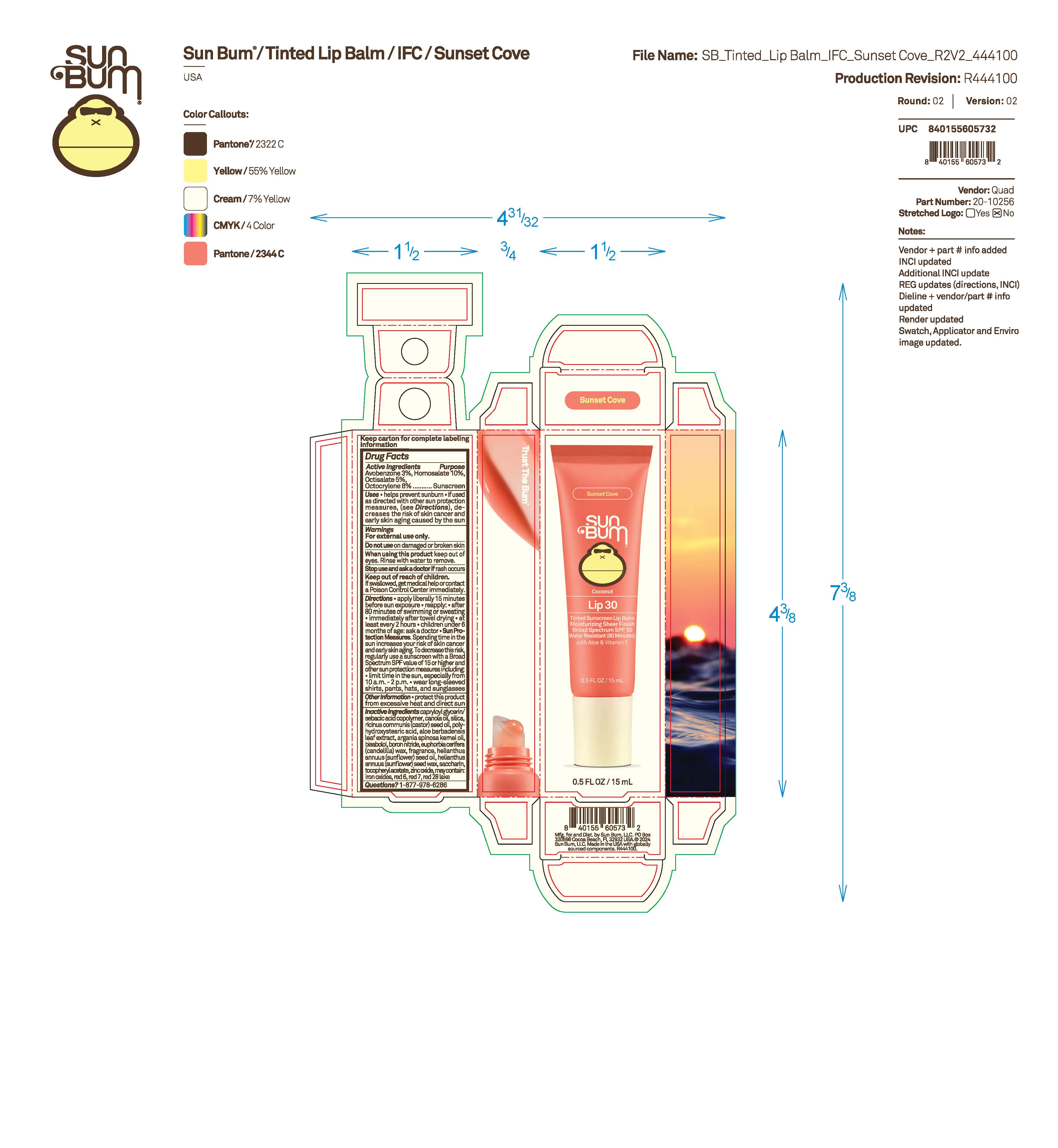 DRUG LABEL: Sun Bum Coconut Lip 30 Tinted Sunscreen Lip Balm - Bonfire
NDC: 69039-830 | Form: OINTMENT
Manufacturer: Sun Bum, LLC
Category: otc | Type: HUMAN OTC DRUG LABEL
Date: 20250828

ACTIVE INGREDIENTS: AVOBENZONE 30 mg/1 mL; OCTISALATE 50 mg/1 mL; OCTOCRYLENE 80 mg/1 mL; HOMOSALATE 100 mg/1 mL
INACTIVE INGREDIENTS: CAPRYLOYL GLYCERIN/SEBACIC ACID COPOLYMER (2000 MPA.S); ARGANIA SPINOSA KERNEL OIL; EUPHORBIA CERIFERA (CANDELILLA) WAX; POLYHYDROXYSTEARIC ACID (2300 MW); ZINC OXIDE; FERRIC OXIDE RED; CANOLA OIL; RICINUS COMMUNIS (CASTOR) SEED OIL; RED 7; HELIANTHUS ANNUUS SEED WAX; SACCHARIN; ALOE BARBADENSIS LEAF; BISABOLOL; BORON NITRIDE; RED 28; .ALPHA.-TOCOPHEROL ACETATE; SILICA; HELIANTHUS ANNUUS (SUNFLOWER) SEED OIL; RED 6

Sun Bum Coconut Lip 30 Tinted Sunscreen Lip Balm - Bonfire, Cocoa Beach, Sunset Cove, Heat Wave

Active Ingredients

AVOBENZONE 3%, HOMOSALATE 10%, OCTISALATE 5%, OCTOCRYLENE 8%

Purpose

Sunscreen

Uses

• helps prevent sunburn • if used as directed with other sun protection measures, (see Directions) decreases the risk of skin cancer and early skin aging caused by the sun

Warnings

For external use only.

Do not use on damaged or broken skin

When using this product keep out of eyes. Rinse with water to remove.

Stop use and ask a doctor if rash occurs

Keep out of reach of children. If swallowed, get medical help or contact a Poison Control Center immediately.

Warnings

Keep Out Of Reach Of Children

Directions

• apply liberally 15 minutes before sun exposure

• reapply: • after 80 minutes of swimming or sweating • immediately after towel drying • at least every 2 hours

• children under 6 months of age: ask a doctor

• Sun Protection Measures. Spending time in the sun increases your risk of skin cancer and early skin aging. To decrease this risk, regularly use a sunscreen with a Broad Spectrum SPF value of 15 or higher and other sun protection measures including:

• limit time in the sun, especially from 10 a.m.- 2 p.m.

• wear long-sleeved shirts, pants, hats and sunglasses

Directions

• apply liberally 15 minutes before sun exposure

Other Information

protect this product from excessive heat and direct sun

Inactive Ingredients

CAPRYLOYL GLYCERIN/SEBACIC ACID COPOLYMER, CANOLA OIL, SILICA, RICINUS COMMUNIS (CASTOR) SEED OIL, POLYHYDROXYSTEARIC ACID, ALOE BARBADENSIS LEAF EXTRACT, ARGANIA SPINOSA KERNEL OIL, BISABOLOL, BORON NITRIDE, EUPHORBIA CERIFERA (CANDELILLA) WAX, FRAGRANCE, HELIANTHUS ANNUUS (SUNFLOWER) SEED OIL, HELIANTHUS ANNUUS (SUNFLOWER) SEED WAX, SACCHARIN, TOCOPHEROL ACETATE, ZINC OXIDE, MAY CONTAIN: IRON OXIDES, RED 6, RED 7, RED 28 LAKE

Questions?

1-877-978-6286